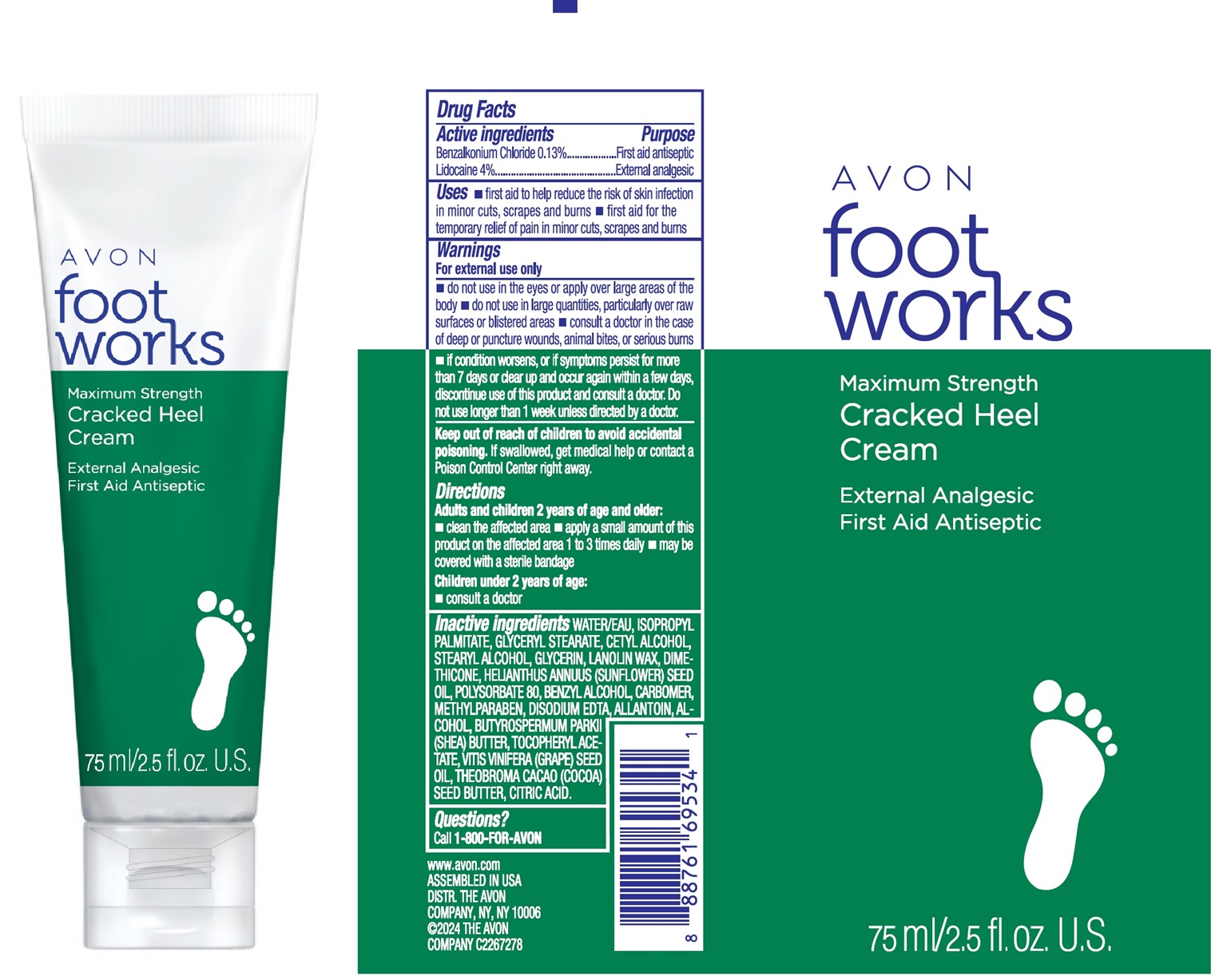 DRUG LABEL: AVON footworks Maximum Strength Cracked Heel
NDC: 10096-4002 | Form: CREAM
Manufacturer: The Avon Company
Category: otc | Type: HUMAN OTC DRUG LABEL
Date: 20240801

ACTIVE INGREDIENTS: LIDOCAINE 40 mg/1 mL; BENZALKONIUM CHLORIDE 1.3 mg/1 mL
INACTIVE INGREDIENTS: WATER

AVON footworks Maximum Strength Cracked Heel Cream

Active Ingredient

Benzalkonium Chloride 0.13%
Lidocaine 4%

Purpose

First aid antiseptic
External analgesic

Uses

- first aid to help reduce the risk of skin infection in minor cuts, scraps and burns
- first aid for the temporary relief of pain in minor cuts, scrapes and burns

Warnings

For external use only

- do not use in the eyes or apply over large areas of the body
- do not use in large quantities, particularly over raw surfaces or blistered areas
- consult a doctor in the case of deep or puncture wounds, animal bites, or serious burns
- if condition worsens, of if symptoms persist for more than 7 days or clear up and occur again within a few days, discontinue use of this product and consult a doctor. Do not use longer than 1 week unless directed by a doctor.

Keep out of reach of children to avoid accidental poisoning.

If swallowed, get medical help or contact a Poison Control Center right away.

Directions

Adults and children 2 years of age and older:

- clean the affected are
- apply a small amount of this product on the affected are 1 to 3 times daily
- may be covered with a sterile bandage

Children under 2 years of age:

- consult a doctor

Inactive Ingredients

Water, Isopropyl Palmitate, Glyceryl Stearate, Cetyl Alcohol, Stearyl Alcohol, Glycerin, Lanolin Wax, Dimethicone, Helianthus Annuus (Sunflower) Seed Oil, Polysorbate 80, Benzyl Alcohol, Carbomer, Methylparaben, Disodium EDTA, Allantoin, Alcohol, Butyrospermum Parkii (Shea) Butter, Tocopheryl Acetate, Vitis Vinifera (Grape) Seed Oil, Theobroma Cacao (Cocoa) Seed Butter, Citric Acid

Questions?

Call 1-800-FOR-AVON

www.avon.com
ASSEMBLED IN USA
DISTR. THE AVON
COMPANY, NY, NY 1006
© 2024 THE AVON
COMPANY C2267278

Principal Display Panel

AVON
foot
works
Maximum Strength
Cracked Heel
Cream
External Analgesic
First Aid Antiseptic
75ml / 2.5 fl.oz. U.S.